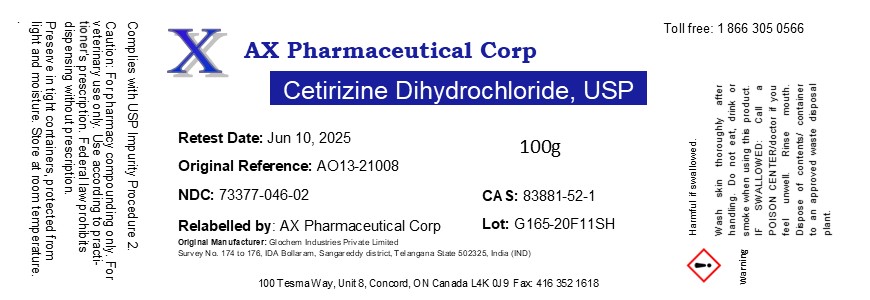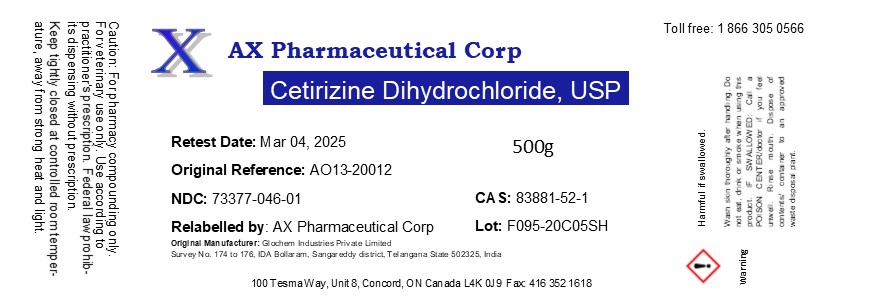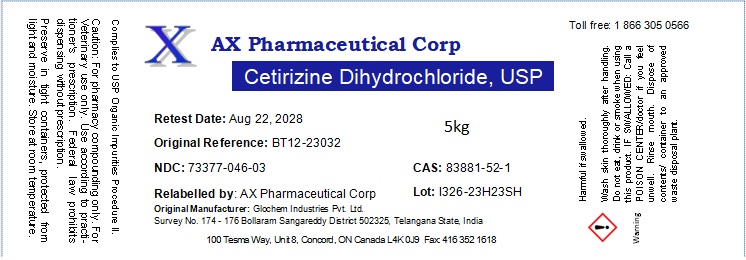 DRUG LABEL: Cetirizine Dihydrochloride
NDC: 73377-046 | Form: POWDER
Manufacturer: AX Pharmaceutical Corp
Category: other | Type: BULK INGREDIENT - ANIMAL DRUG
Date: 20231110

ACTIVE INGREDIENTS: CETIRIZINE HYDROCHLORIDE 1 g/1 g

Cetirizine Dihydrochloride